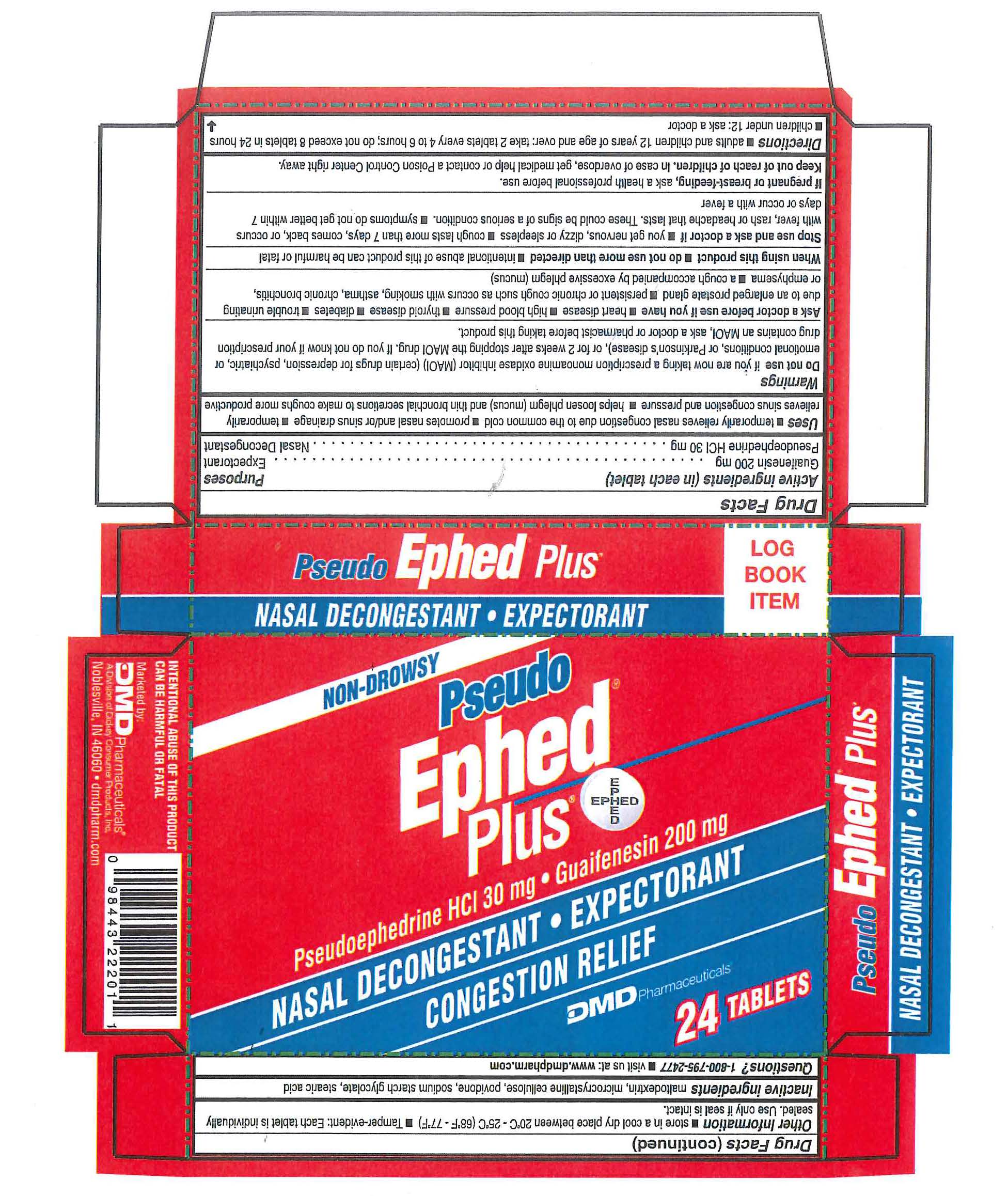 DRUG LABEL: Pseudo Ephed Plus
NDC: 65193-325 | Form: TABLET
Manufacturer: Dickey Consumer Products DBA DMD
Category: otc | Type: HUMAN OTC DRUG LABEL
Date: 20190320

ACTIVE INGREDIENTS: PSEUDOEPHEDRINE HYDROCHLORIDE 30 mg/1 1; GUAIFENESIN 200 mg/1 1
INACTIVE INGREDIENTS: POVIDONE K30; STEARIC ACID; CELLULOSE, MICROCRYSTALLINE; SODIUM STARCH GLYCOLATE TYPE A POTATO; MALTODEXTRIN

DRUG FACTS

Active Ingredient(In Each Tablet): Pseudoephedrine HCl 30 mg, Guaifenesin 200 mg

PURPOSE

Purposes - Nassal Decongestant, Expectorant

INDICATIONS AND USAGE

• temporarily relieves nasal congestion due to the common cold • promotes nasal and/or sinus drainage • temporarily relieves sinus congestion and pressure • helps loosen phlegm (mucus) and thin bronchial secretions to make coughs more productive

Do not use: • if you are now taking a prescription monoamine oxidase inhibitor (MAOI) (Certain drugs for depression, psychiatric, or emotional conditions, or Parkinson's disease), or for 2 weeks after stopping the MAOI drug. If you do not know if your prescription drug contains an MAOI, ask a doctor or pharmacist before taking this product.

Ask a doctor before use if you have: • heart disease • high blood pressure • thyroid disease • diabetes • trouble urinating due to an enlarged prostate gland • persistent or chronic cough such as occurs with smoking, asthma, chronic bronchitis, or emphysema • a cough accompanied by excessive phlegm (mucus)

When using this product • do not use more than directed • intentional abuse of this product can be harmful or fatal

Stop use and ask a doctor if: • you get nervous dizzy or sleepless • cough lasts more than 7 days, comes back, or occurs with fever, rash or headache that lasts. These could be signs of a serious condition. • symptoms do not get better within 7 days or occur with a fever

PREGNANCY OR BREAST FEEDING

If pregnant or breast feeding, ask a health proffessional before use.

Keep out of reach of children. In case of overdose, get medical help or contact a Poison Control Center right away.

DOSAGE AND ADMINISTRATION

• adults and children 12 years of age and over: take 2 tablets every 4 to 6 hours; do not exceed 8 tablets in 24 hours • children under 12 years of age: ask a doctor

INACTIVE INGREDIENT

Inactive Ingredients: Maltodextrin, Microcrystalline Cellulose, Povidone, Sodium Starch Glycolate, Stearic Acid